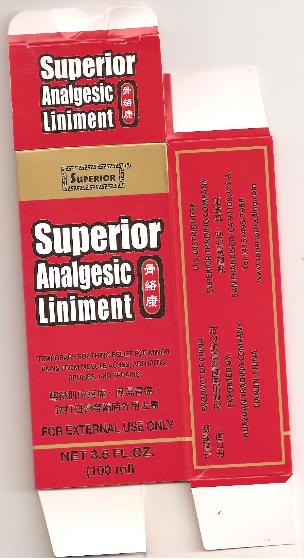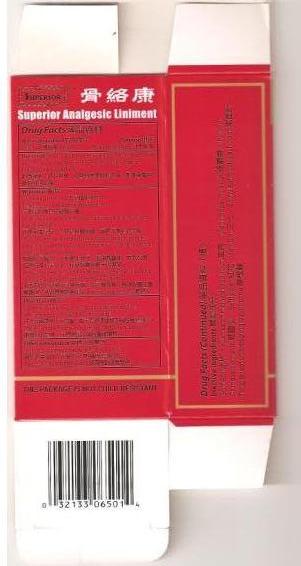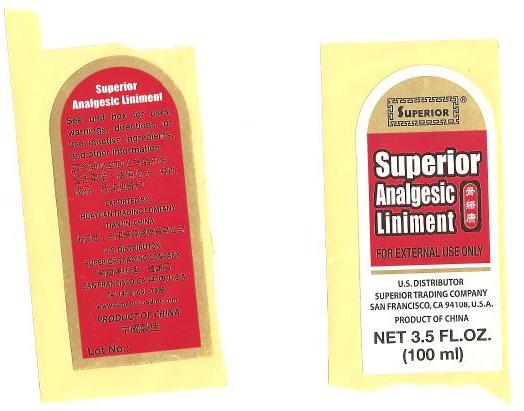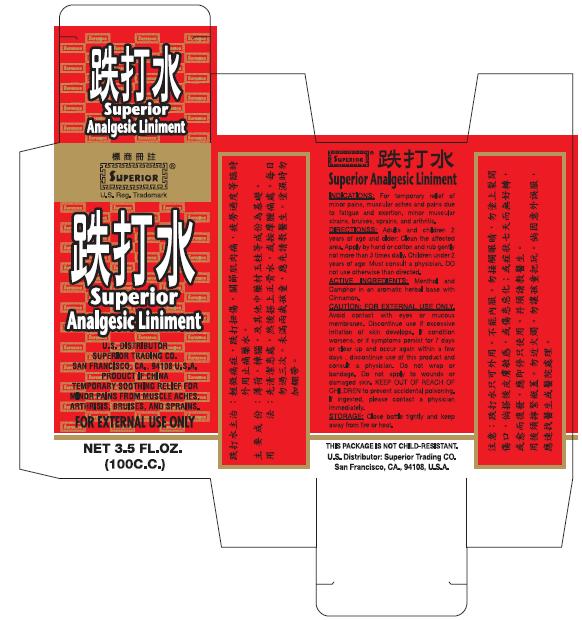 DRUG LABEL: Superior Analgesic
NDC: 58350-000 | Form: LINIMENT
Manufacturer: Superior Trading Company
Category: otc | Type: Human OTC Drug Label
Date: 20091229

ACTIVE INGREDIENTS: MENTHOL 3.5 mg/100 mL
INACTIVE INGREDIENTS: SAFFLOWER

Active Ingredient

Menthol 13.28%

Purpose

External Analgesic

Uses

For temporary relief of minor pains and aches of muscles and joints due to fatigue and exertion, strains, bruises, sprains & arthritis.

Warnings

For external use only.

Do not use

on wounds or damaged skin.

When using this product

avoid contact with eyes & do not bandage tightly.

Stop use and ask a doctor if

condition worsens, symptoms persist for more than 7 days, or symptoms clear up and occur again within a few days.

Keep out of reach of children

If swallowed, get medical help or contact a Poison Control Center right away.

(Poison Control Center)

Directions

Adults and children 2 years of age and older: apply to affected area not more than 3 times daily.

Children under 2 years of age: Do not use. Consult a doctor.

Other information

Store at room temperature under 86º F (30ºC)

Keep container tightly closed. →

Drug Facts (Continued)

Inactive ingredients

Borneol, Kusnezoff monkshood root, Man-made musk, Root of Chinese clematis, Safflower, San Chi, Shinyleaf pricklyash root, Twig & leaf of creeping paychotria

THIS PACKAGE IS NOT CHILD-RESISTANT.

LABEL

Superior Analgesic Liniment

U.S. DISTRIBUTOR

SUPERIOR TRADING COMPANY

SAN FRANCISCO, CA 94108, U.S.A.

PRODUCT OF CHINA

NET 3.5 FL.OZ. (100 ml)

See Unit box for uses, warnings, directions for use, inactive ingredient, and other information.

EXPORTED BY:

HUAYUAN TRADING COMPANY

TIANJIN, CHINA

U.S. DISTRIBUTOR

SUPERIOR TRADING COMPANY

SAN FRANCISCO, CA 94108, U.S.A.

Tel. (415) 495-7988

www.superiortrading.com

PRODUCT OF CHINA

Lot No.:

PACKAGE LABEL.PRINCIPAL DISPLAY PANEL - 100 ml

Superior Analgesic Liniment

TEMPORARY SOOTHING RELIEF FOR MINOR

PAINS FROM MUSCLE ACHES, ARTHRISIS, BRUISES, AND SPRAINS.

FOR EXTERNAL USE ONLY

NET 3.5 FL.OZ. (100 ml)

PRODUCT OF CHINA

EXPORTED BY:

HUAYUAN TRADING COMPANY

TIANJIN, CHINA

U.S. DISTRIBUTOR

SUPERIOR TRADING COMPANY

SAN FRANCISCO, CA 94108, U.S.A.

Tel. (415) 495-7988

www.superiortrading.com

PACKAGE LABEL.PRINCIPAL DISPLAY PANEL - 100 ml

Superior Analgesic Liniment

FOR EXTERNAL USE ONLY

U.S. DISTRIBUTOR

SUPERIOR TRADING COMPANY

SAN FRANCISCO, CA 94108, U.S.A.

PRODUCT OF CHINA

NET 3.5 FL.OZ. (100 ml)

PACKAGE LABEL.PRINCIPAL DISPLAY PANEL - 100 c.c.

Superior Analgesic Liniment

U.S. DISTRIBUTOR

SUPERIOR TRADING CO.

SAN FRANCISCO, CA 94108, U.S.A.

PRODUCT OF CHINA

TEMPORARY SOOTHING RELIEF FOR MINOR

PAINS FROM MUSCLE ACHES, ARTHRISIS, BRUISES, AND SPRAINS.

FOR EXTERNAL USE ONLY

NET 3.5 FL.OZ. (100 C.C.)